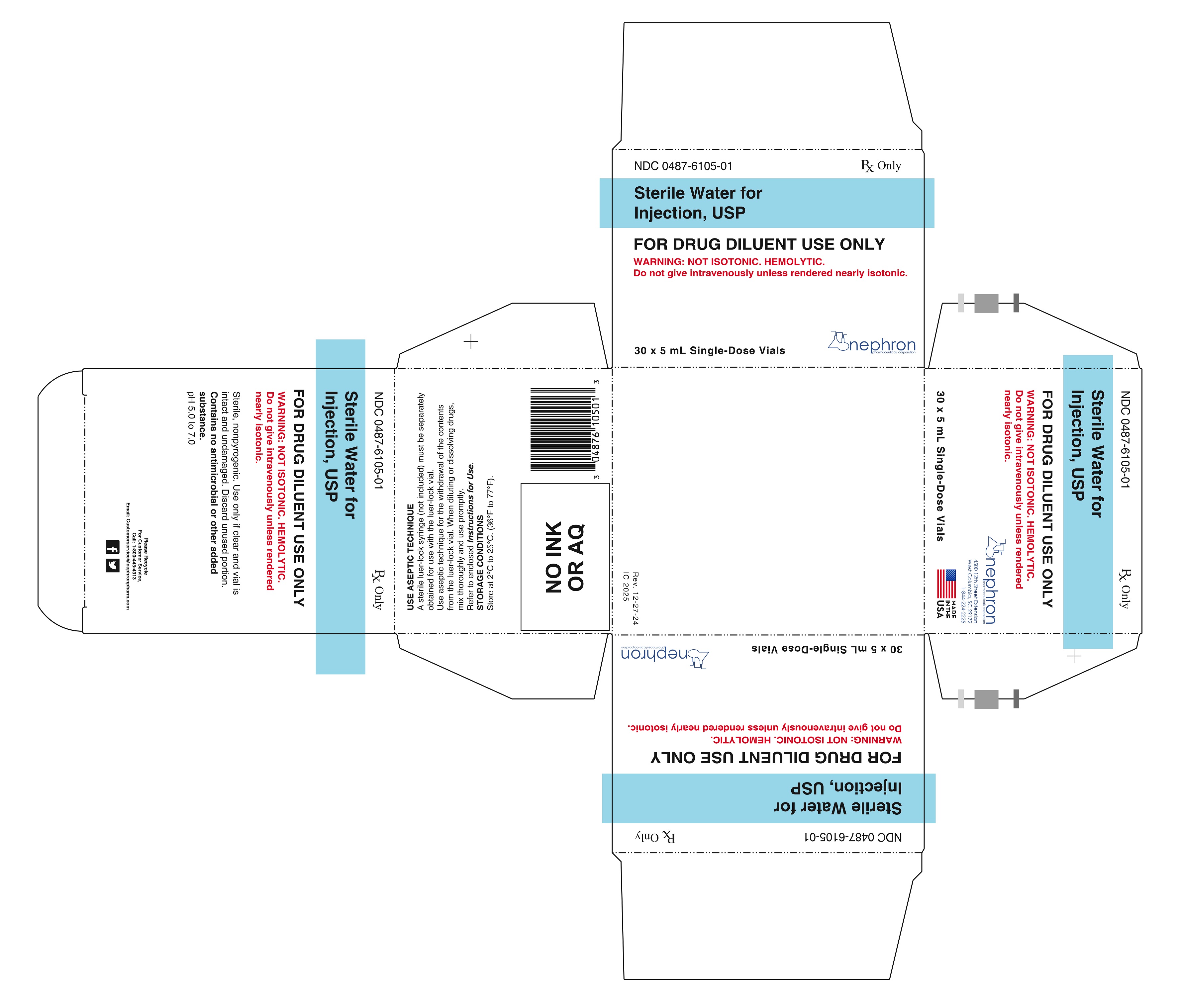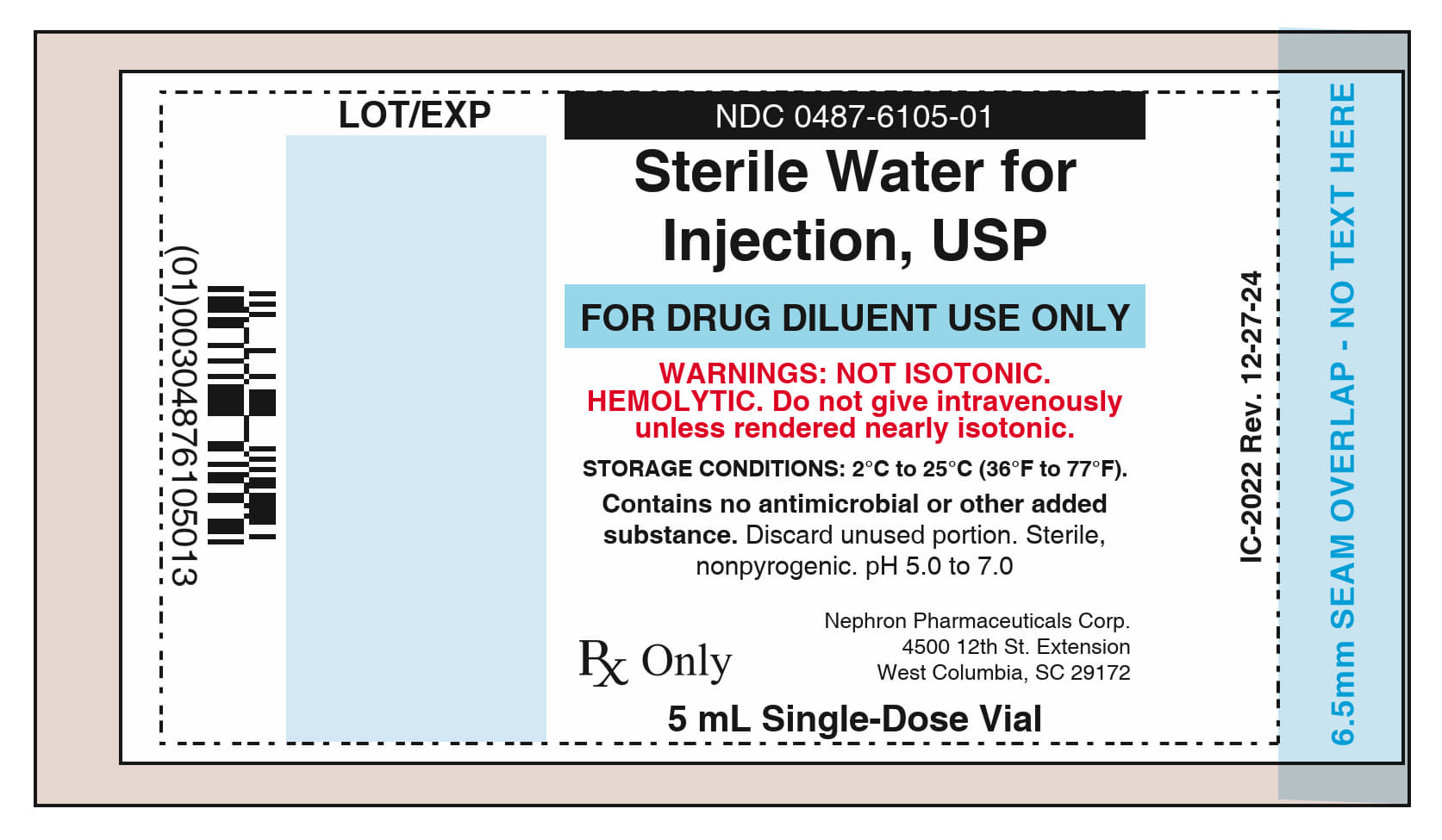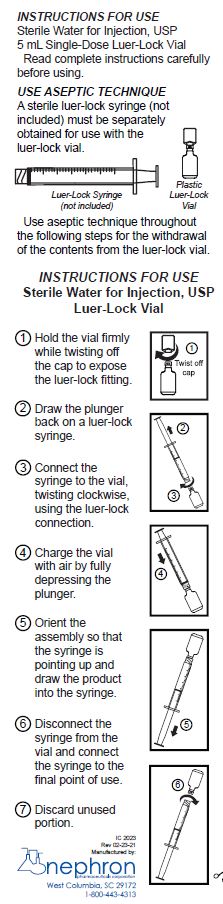 DRUG LABEL: Sterile Water
NDC: 0487-6105 | Form: INJECTION
Manufacturer: Nephron Pharmaceuticals Corporation
Category: prescription | Type: HUMAN PRESCRIPTION DRUG LABEL
Date: 20250711

ACTIVE INGREDIENTS: WATER 1 mL/1 mL

Sterile Water for Injection, USP
For Drug Diluent Use Only
Rx Only
Sterile
Plastic Single-Dose Luer-Lock Vial

DESCRIPTION

This preparation is designed solely for parenteral use, only after addition of drugs that require dilution or must be dissolved in an aqueous vehicle prior to injection.

Sterile Water for Injection, USP is a sterile, nonpyrogenic preparation of water for injection, which contains no bacteriostat, antimicrobial agent or added buffer, and is supplied only in single-dose containers to dilute or dissolve drugs for injection. For intravenous injection, dissolve sufficient solute to make an approximately isotonic solution. Water for Injection, USP is chemically designated H2O. pH 5.0 to 7.0.

The plastic single-dose vial is fabricated from polypropylene resin. The plastic vials feature a twist-off cap which, when removed, allows access to a luer-lock fitting for connection to a luer-lock syringe. The twist-off cap is a one-time use tamper evident feature, and the container vial cannot be reclosed once the cap is removed.

CLINICAL PHARMACOLOGY

Water is an essential constituent of all body tissues and accounts for approximately 70% of total body weight.

Average adult daily requirement ranges from two to three liters (1.0 to 1.5 liters each for insensible water loss by perspiration and urine production).

Water balance is maintained by various regulatory mechanisms. Water for distribution depends primarily on the concentration of electrolytes in the body compartments and sodium (Na+) plays a major role in maintaining physiologic equilibrium.

The small volume of fluid provided by Sterile Water for Injection when used only as a pharmaceutical aid for diluting or dissolving drugs for parenteral injection, is unlikely to exert a significant effect on fluid balance except possibly in neonates or very small infants.

INDICATIONS AND USAGE

This parenteral preparation is indicated only for diluting or dissolving drugs for intravenous, intramuscular, or subcutaneous injection, according to instructions of the manufacturer of the drug to be administered.

CONTRAINDICATIONS

Sterile Water for Injection must be made approximately isotonic prior to use.

WARNINGS

Intravenous administration of Sterile Water for Injection without a solute may result in hemolysis.

Do not use for intravenous injection unless the osmolar concentration of additives results in an approximate isotonic admixture.

Consult the manufacturer’s instructions for choice of vehicle, appropriate dilution, or volume for dissolving the drugs to be injected, including the route and rate of injection.

Inspect reconstituted (diluted or dissolved) drugs for clarity (if soluble) and freedom from unexpected precipitation or discoloration prior to administration.

PREGNANCY

Animal reproduction studies have not been conducted with Sterile Water for Injection. It is not known whether sterile water containing additives can cause fetal harm when administered to a pregnant woman or affect reproduction capacity. Sterile Water for Injection with additives should be given to a pregnant woman only if clearly needed.

PEDIATRIC USE

Safety and effectiveness have been established in pediatric patients. However, in neonates or very small infants, the volume of fluid may affect fluid and electrolyte balance.

DRUG INTERACTIONS

Some drugs for injection may be incompatible in a given vehicle, when combined in the same vehicle, or in a vehicle containing benzyl alcohol. Consult with pharmacist, if available.

Use aseptic technique for withdrawal from the container. When diluting or dissolving drugs, mix thoroughly and use promptly.

Do not store reconstituted solutions of drugs for injection unless otherwise directed by the manufacturer of the solute. Do not use unless the solution is clear.

Do not reuse single-dose containers. Discard unused portion.

ADVERSE REACTIONS

Reactions which may occur because of this solution, added drugs, or the technique of reconstitution or administration include febrile response, local tenderness, abscess, tissue necrosis or infection at the site of injection, venous thrombosis, or phlebitis extending from the site of injection and extravasation.

If an adverse reaction does occur, discontinue the infusion, evaluate the patient, institute appropriate countermeasures, and if possible, retrieve and save the remainder of the unused vehicle for examination.

OVERDOSAGE

Use only as a diluent or solvent. This parenteral preparation is unlikely to pose a threat of fluid overload, except possibly in neonates or very small infants. In the event these should occur, re-evaluate the patient and institute appropriate corrective measures. See WARNINGS, PRECAUTIONS and ADVERSE REACTIONS.

DOSAGE AND ADMINISTRATION

The volume of the preparation to be used for diluting or dissolving any drug for injection is dependent on the vehicle concentration, dose, and route of administration as recommended by the manufacturer. This parenteral should be inspected visually for particulate matter and discoloration prior to administration, whenever solution and container permit. Please refer to INSTRUCTIONS FOR USE for administration instructions.

HOW SUPPLIED

Sterile Water for Injection, USP is supplied in 5 mL vials, packaged in cartons as follows: NDC 0487-6105-01, 30 individual 5 mL single-dose luer-lock vials.

Discard unused portion. Each vial is made from a polypropylene (PP) resin. Store at 2°C to 25°C (36°F to 77°F).

INSTRUCTIONS FOR USE

Sterile Water for Injection, USP 5 mL Single-Dose Luer-Lock Vial Read complete instructions carefully before using. USE ASEPTIC TECHNIQUE and instructions for use. A sterile luer-lock syringe (not included) must be separately obtained for use with the luer-lock vial. Use aseptic technique throughout the Infor the withdrawal of the contents from the luer-lock vial.